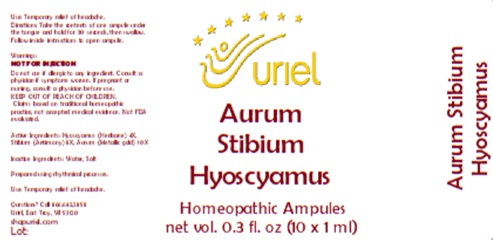 DRUG LABEL: Aurum Stibium Hyoscyamus
NDC: 48951-1405 | Form: LIQUID
Manufacturer: Uriel Pharmacy, Inc
Category: homeopathic | Type: HUMAN OTC DRUG LABEL
Date: 20260116

ACTIVE INGREDIENTS: ANTIMONY 8 [hp_X]/1 mL; HYOSCYAMUS NIGER LEAF 4 [hp_X]/1 mL; GOLD 10 [hp_X]/1 mL
INACTIVE INGREDIENTS: WATER; SODIUM CHLORIDE

Aurum Stibium Hyoscyamus

PURPOSE

Use: Temporary relief of headache.

INDICATIONS AND USAGE

FOR ORAL USE ONLY

DOSAGE AND ADMINISTRATION

Take the contents of one ampule under the
tongue and hold for 30 seconds, then swallow.

Follow inside instructions to open ampule.

Warnings:

NOT FOR INJECTION

Do not use if allergic to any ingredient. Consult a physician if symptoms worsen. If pregnant or nursing, consult a physician before use.

Claims based on traditional homeopathic practice, not accepted medical evidence. Not FDA evaluated.

KEEP OUT OF REACH OF CHILDREN.

ACTIVE INGREDIENT

Active Ingredients: Hyoscyamus (Henbane) 4X, Stibium (Antimony) 8X, Aurum (Metallic gold) 10X

Inactive Ingredients: Water, Salt

Prepared using rhythmical processes.

Questions? Call 866.642.2858
Uriel, East Troy, WI 53120
shopuriel.com

Lot: